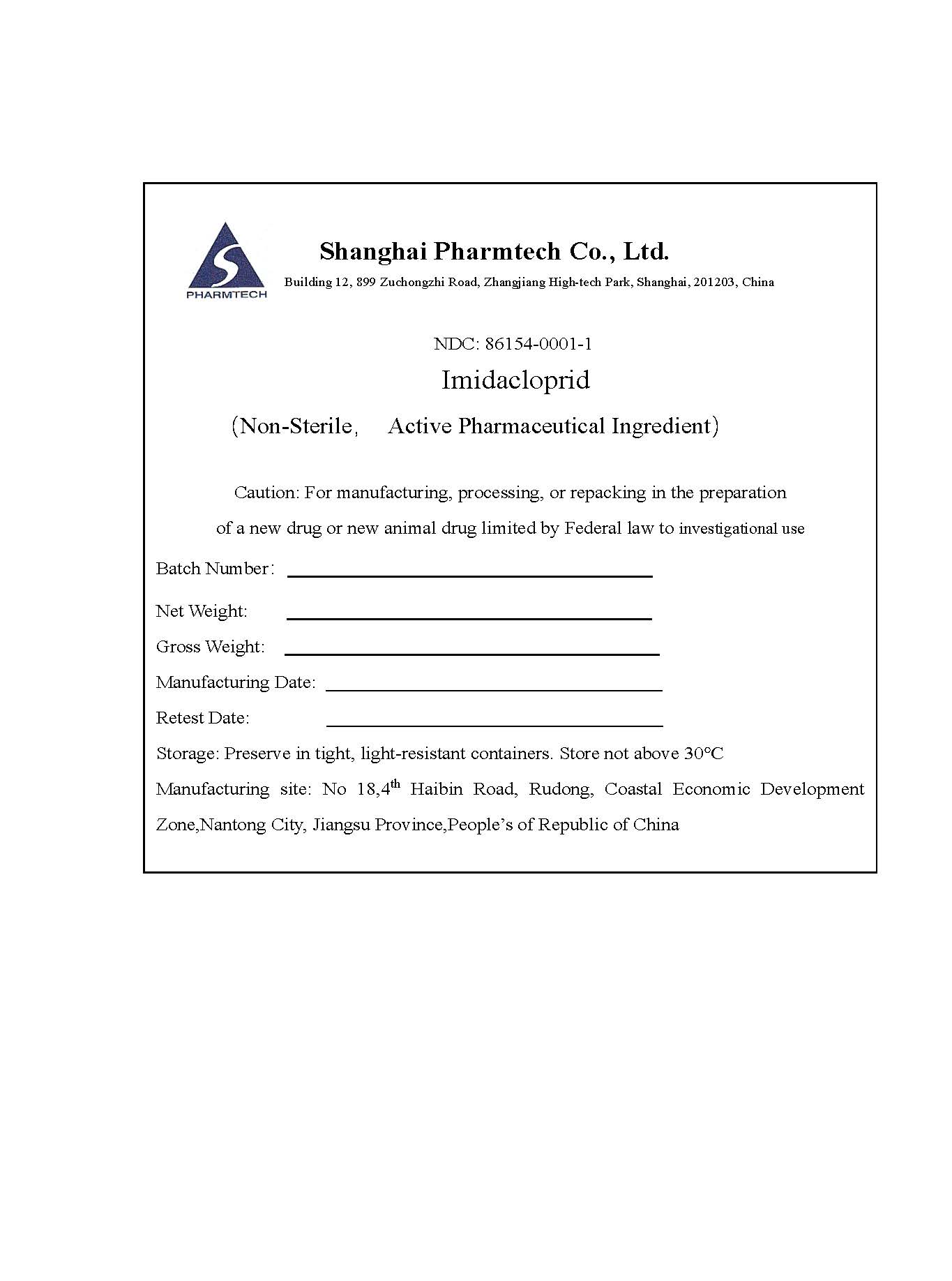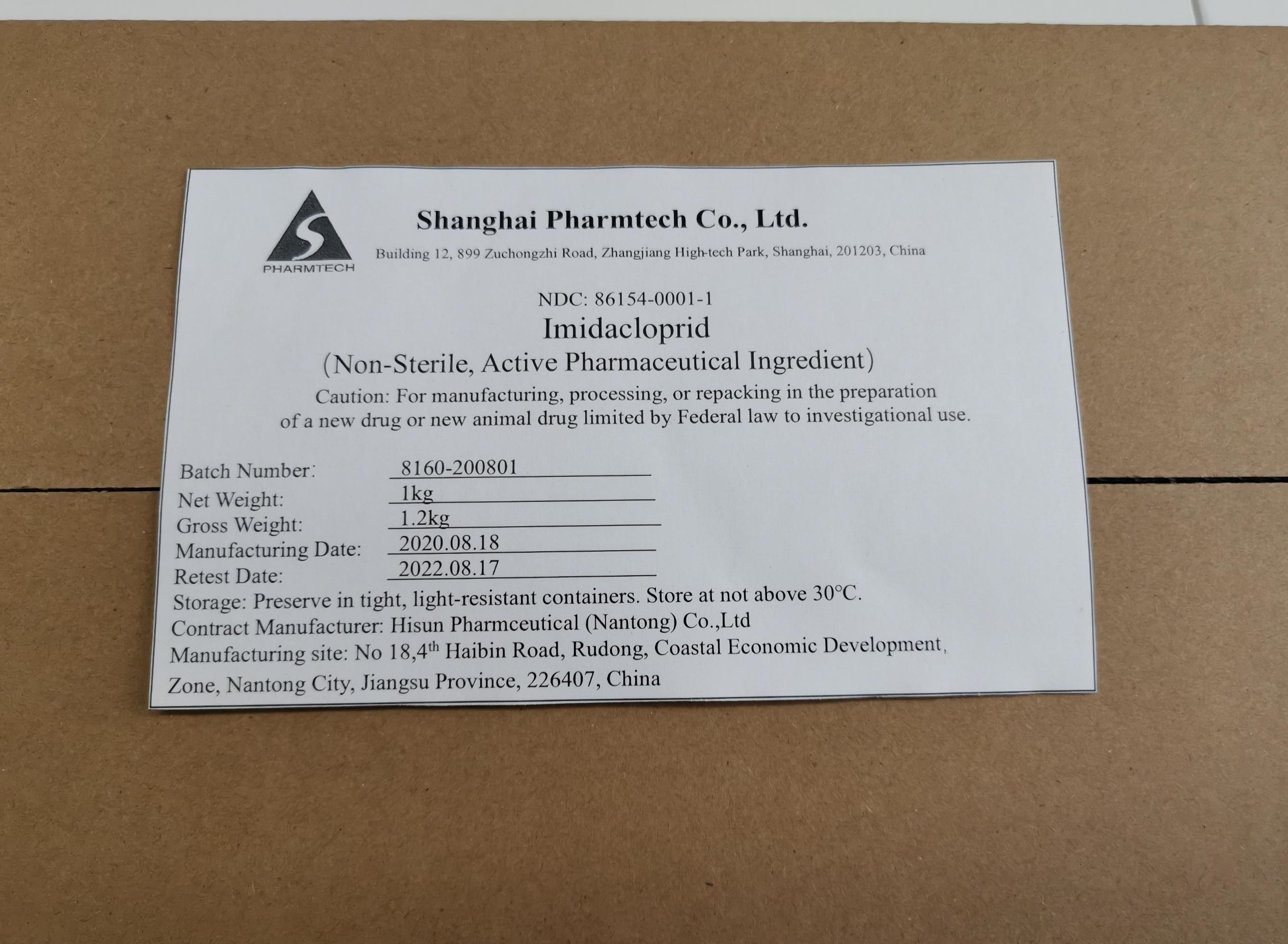 DRUG LABEL: Imidacloprid
NDC: 86154-0001 | Form: POWDER
Manufacturer: Shanghai Pharmtech Co.,Ltd
Category: other | Type: BULK INGREDIENT - ANIMAL DRUG
Date: 20220222

ACTIVE INGREDIENTS: IMIDACLOPRID 1 kg/1 kg

Imidacloprid SPL

Image of Imidaclorid 1Kg NDC label

Image of representative sample of container label